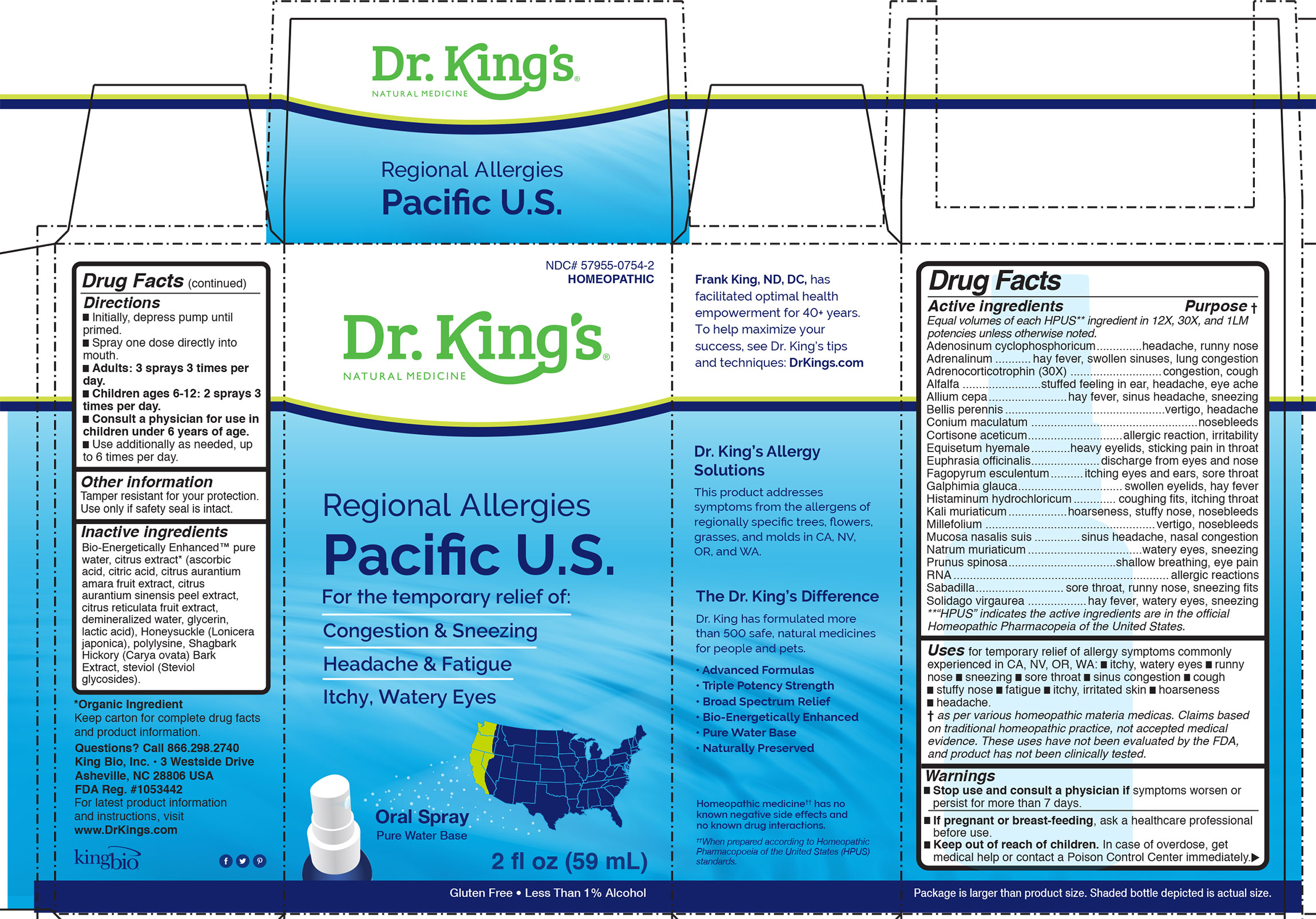 DRUG LABEL: Regional Allergies Pacific US
NDC: 57955-0754 | Form: LIQUID
Manufacturer: King Bio Inc.
Category: homeopathic | Type: HUMAN OTC DRUG LABEL
Date: 20200708

ACTIVE INGREDIENTS: ADENOSINE CYCLIC PHOSPHATE 12 [hp_X]/59 mL; EPINEPHRINE 12 [hp_X]/59 mL; CORTICOTROPIN 30 [hp_X]/59 mL; ALFALFA 12 [hp_X]/59 mL; ONION 12 [hp_X]/59 mL; BELLIS PERENNIS 12 [hp_X]/59 mL; CONIUM MACULATUM FLOWERING TOP 12 [hp_X]/59 mL; CORTISONE ACETATE 12 [hp_X]/59 mL; EQUISETUM HYEMALE 12 [hp_X]/59 mL; EUPHRASIA STRICTA 12 [hp_X]/59 mL; FAGOPYRUM ESCULENTUM 12 [hp_X]/59 mL; GALPHIMIA GLAUCA FLOWERING TOP 12 [hp_X]/59 mL; HISTAMINE DIHYDROCHLORIDE 12 [hp_X]/59 mL; POTASSIUM CHLORIDE 12 [hp_X]/59 mL; ACHILLEA MILLEFOLIUM 12 [hp_X]/59 mL; SUS SCROFA NASAL MUCOSA 12 [hp_X]/59 mL; SODIUM CHLORIDE 12 [hp_X]/59 mL; PRUNUS SPINOSA FLOWER BUD 12 [hp_X]/59 mL; SACCHAROMYCES CEREVISIAE RNA 12 [hp_X]/59 mL; SCHOENOCAULON OFFICINALE SEED 12 [hp_X]/59 mL; SOLIDAGO VIRGAUREA FLOWERING TOP 12 [hp_X]/59 mL
INACTIVE INGREDIENTS: WATER; CARYA OVATA BARK; CITRUS BIOFLAVONOIDS; LONICERA JAPONICA FLOWER; POLYEPSILON-LYSINE (4000 MW); REBAUDIOSIDE A

Regional Allergies Pacific U.S.

ACTIVE INGREDIENT

Adenosinum cyclophosphoricum, Adrenalinum, Adrenocorticotrophin (30X), Alfalfa, Allium cepa, Bellis perennis, Conium maculatum, Cortisone aceticum, Equisetum hyemale, Euphrasia officinalis, Fagopyrum esculentum, Galphimia glauca, Histaminum hydrochloricum, Kali muriaticum, Millefolium, Mucosa nasalis suis, Natrum muriaticum, Prunus spinosa, RNA, Sabadilla, Solidago virgaurea.
Equal volumes of each ingredient in 12X, 30X, 1LM potencies unless otherwise noted.

INDICATIONS AND USAGE

Uses for temporary relief of allergy symptoms commonly experienced in CA, NV, OR, WA: •itchy, watery eyes •runny nose •sneezing •sore throat •sinus congestion •cough •stuffy nose •fatigue •itchy, irritated skin •hoarseness •headache.

Stop use and consult a physician if symptoms worsen or
persist for more than 7 days.

PREGNANCY OR BREAST FEEDING

If pregnant or breast-feeding, ask a healthcare professional
before use.

Keep out of reach of children. In case of overdose, get
medical help or contact a Poison Control Center immediately.

Directions

- Initially, depress pump until primed.
- Spray one dose directly into mouth.
- Adults: 3 sprays 3 times per day.
- Children ages 6-12: 2 sprays 3 times per day.
- Consult a physician for use in children under 6 years of age.
- Use additionally as needed, up to 6 times per day.

Other information
Tamper resistant for your protection.
Use only if safety seal is intact.

Inactive ingredients
Bio-Energetically Enhanced™ pure
water, citrus extract* (ascorbic
acid, citric acid, citrus aurantium
amara fruit extract, citrus
aurantium sinensis peel extract,
citrus reticulata fruit extract,
demineralized water, glycerin,
lactic acid), Honeysuckle (Lonicera
japonica), polylysine, Shagbark
Hickory (Carya ovata) Bark
Extract, steviol (Steviol
glycosides).

Drug Facts

__________________________________________________________________________________________________________

HPUS active ingredients Purpose

Equal volumes of each ingredient in 12X, 30X, 1LM potencies unless otherwise noted.

Adenosinum cyclophosphoricum...........................headache, runny nose

Adrenalinum.........................hay fever, swollen sinuses, lung congestion

Adrenocorticotrophin(30X).........................................congestion, cough

Alfalfa....................................stuffed feeling in ear, headache, eye ache

Allium cepa.....................................hay fever, sinus headache, sneezing

Bellis perennis..........................................................vertigo, headache

Conium maculatum.............................................................nosebleeds

Cortisone aceticum......................................allergiec reaction, irritability

Equisetum hyemale..........................heavy eyelids, sticking pain in throat

Euphrasia officinalis...................................discharge from eyes and nose

Fagopyrum esculentum.........................itching eyes and ears, sore throat

Galphimia glauca............................................swollen eyelids, hay fever

Histaminum hydrochloricum...........................coughing fits, itching throat

Kali muriaticum..................................hoarseness, stuffy nose, nosebleed

Millefolium..............................................................vertigo, nosebleeds

Mucosa nasais suis................................sinus headache, nasal congestion

Natrum muriaticum..............................................watery eyes, sneezing

Prunus spinosa.............................................shallow breathing, eye pain

RNA.........................................................................allergiec reactions

Sabadilla.......................................sore throat, runny nose, sneezing fits

Solidago virgaurea................................hay fever, watery eyes, sneezing

*"HPUS" indicates the active ingredients are in the official Homeopathic Pharmacopeia of the United States.